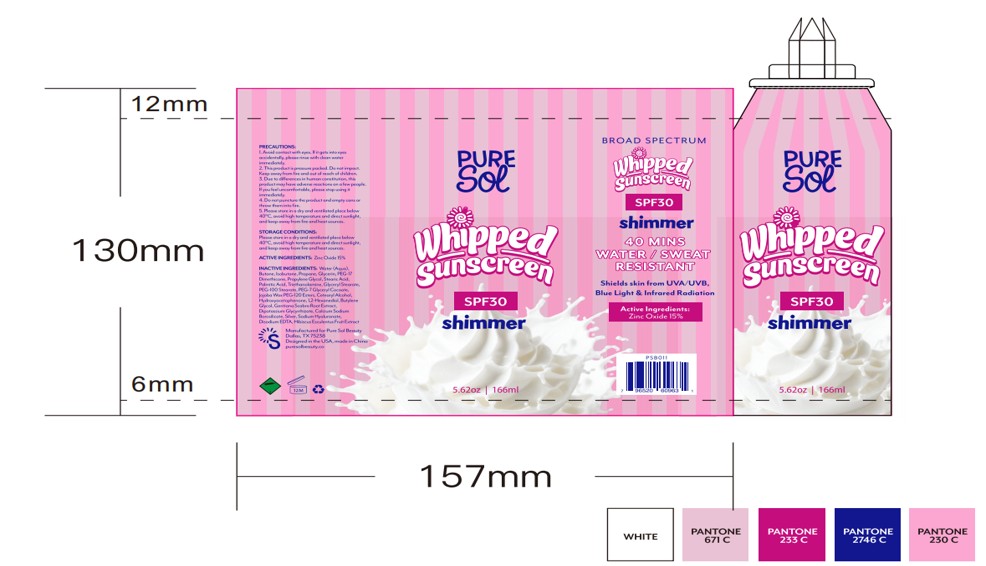 DRUG LABEL: PURE SOL SPF 30 Mineral Whipped Sunscreen (Shimmer)
NDC: 84090-002 | Form: SPRAY
Manufacturer: Brand 2022b LLC
Category: otc | Type: HUMAN OTC DRUG LABEL
Date: 20251004

ACTIVE INGREDIENTS: ZINC OXIDE 15 g/100 mL
INACTIVE INGREDIENTS: STEARIC ACID; TRIETHANOLAMINE; OKRA; CALCIUM SODIUM BOROSILICATE; HYALURONATE SODIUM; ISOBUTANE; 1,2-HEXANEDIOL; SILVER; WATER; GLYCERIN; BUTANE; CETOSTEARYL ALCOHOL; GENTIANA SCABRA ROOT; EDETATE DISODIUM; HYDROGENATED JOJOBA OIL/JOJOBA OIL, RANDOMIZED (IODINE VALUE 64-70); HYDROXYACETOPHENONE; BUTYLENE GLYCOL; GLYCERYL MONOSTEARATE; PEG-100 STEARATE; PEG-7 GLYCERYL COCOATE; DIPOTASSIUM GLYCYRRHIZATE; PROPANE; PROPYLENE GLYCOL; PALMITIC ACID; PEG-12 DIMETHICONE

84090-002-01.PURE SOL SPF 30 Mineral Whipped Sunscreen(Shimmer)- Spray 166ml

ACTIVE INGREDIENT

Zinc Oxide-15%

PURPOSE

helps prevent sunburn • higher SPF gives more sunburn - protection • helps protect the skin against the harmful effects of - UVA and UVB rays

Keep out of reach of children.

If swallowed, get medical help or
contact a Poison Control Center immediately.

WARNINGS

For external use only

When using this product

avoid contact with the eyes. If contact
occurs rinse thoroughly with water.

Stop use and ask a doctor if

rash or irritation develops and lasts.

INDICATIONS AND USAGE

apply generously and evenly to all exposed areas before sun
exposure • reapply as needed or after towel drying, swimming,
perspiring or vigorous activity • children under 6 months of age:
ask a doctor

INACTIVE INGREDIENT

Water (Aqua)
Butane
Isobutane
Propane
Glycerin
PEG-17 Dimethicone
Propylene Glycol
Stearic Acid
Palmitic Acid
Triethanolamine
Glyceryl Stearate
PEG-100 Stearate
PEG-7 Glyceryl Cocoate
Jojoba Wax PEG-120 Esters
Cetearyl Alcohol
Hydroxyacetophenone
1,2-Hexanediol
Butylene Glycol
Gentiana Scabra Root Extract
Dipotassium Glycyrrhizate
Calcium SodiumBorosilicate
Silver
Sodium Hyaluronate
Disodium EDTA
Hibiscus Esculentus Fruit Extract

DOSAGE AND ADMINISTRATION

Apply generously and evenly over whole body 20 minutes before sun exposure. Reapply frequently.